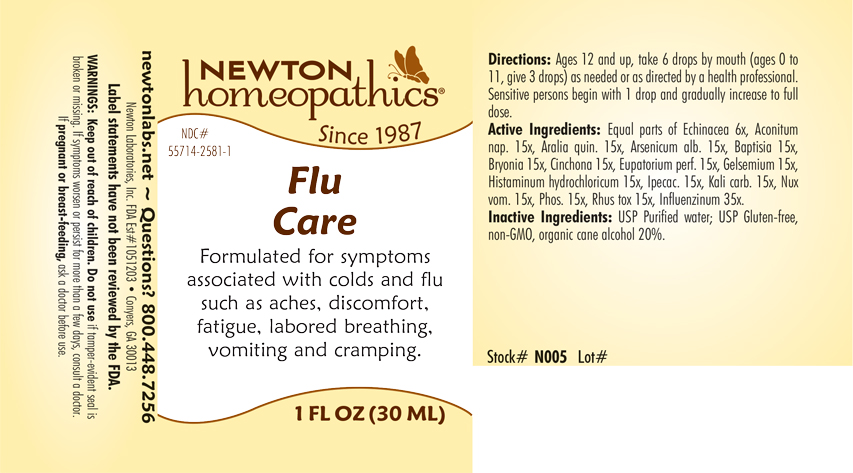 DRUG LABEL: Flu Care
NDC: 55714-2581 | Form: LIQUID
Manufacturer: Newton Laboratories, Inc.
Category: homeopathic | Type: HUMAN OTC DRUG LABEL
Date: 20240214

ACTIVE INGREDIENTS: HISTAMINE DIHYDROCHLORIDE 15 [hp_X]/1 mL; ACONITUM NAPELLUS 15 [hp_X]/1 mL; AMERICAN GINSENG 15 [hp_X]/1 mL; ARSENIC TRIOXIDE 15 [hp_X]/1 mL; BAPTISIA TINCTORIA ROOT 15 [hp_X]/1 mL; BRYONIA ALBA ROOT 15 [hp_X]/1 mL; CINCHONA OFFICINALIS BARK 15 [hp_X]/1 mL; EUPATORIUM PERFOLIATUM FLOWERING TOP 15 [hp_X]/1 mL; GELSEMIUM SEMPERVIRENS ROOT 15 [hp_X]/1 mL; IPECAC 15 [hp_X]/1 mL; POTASSIUM CARBONATE 15 [hp_X]/1 mL; STRYCHNOS NUX-VOMICA SEED 15 [hp_X]/1 mL; PHOSPHORUS 15 [hp_X]/1 mL; TOXICODENDRON PUBESCENS LEAF 15 [hp_X]/1 mL; ECHINACEA, UNSPECIFIED 6 [hp_X]/1 mL; INFLUENZA A VIRUS 35 [hp_X]/1 mL; INFLUENZA B VIRUS 35 [hp_X]/1 mL
INACTIVE INGREDIENTS: WATER; ALCOHOL

Flu 2581L

INDICATIONS & USAGE SECTION

Formulated for symptoms associated with colds and flu such as aches, discomfort, fatigue, labored breathing, vomiting and cramping.

DOSAGE & ADMINISTRATION SECTION

Directions: Ages 12 and up, take 6 drops by mouth (ages 0 to 11, give 3 drops) as needed or as directed by a health professional. Sensitive persons begin with 1 drop and gradually increase to full dose.

OTC - ACTIVE INGREDIENT SECTION

Equal parts of Echinacea 6x, Aconitum nap. 15x, Aralia quin. 15x, Arsenicum alb. 15x, Baptisia 15x, Bryonia 15x, Cinchona 15x, Eupatorium perf. 15x, Gelsemium 15x, Histaminum hydrochloricum 15x, Ipecac. 15x, Kali carb. 15x, Nux vom. 15x, Phos. 15x, Rhus tox. 15x, Influenzinum 35x.

OTC - PURPOSE SECTION

Formulated for symptoms associated with colds and flu such as aches, discomfort, fatigue, labored breathing, vomiting and cramping.

INACTIVE INGREDIENT SECTION

Inactive Ingredients: USP Purified Water; USP Gluten-free, non-GMO, organic cane alcohol 20%.

QUESTIONS SECTION

newtonlabs.net – Questions? 800.448.7256

Newton Laboratories, Inc. FDA Est # 1051203 - Conyers, GA 30013

WARNINGS SECTION

WARNINGS: Keep out of reach of children. Do not use if tamper-evident seal is broken or missing. If symptoms worsen or persist for more than a few days, consult a doctor. If pregnant or breast-feeding, ask a doctor before use.

OTC - PREGNANCY OR BREAST FEEDING SECTION

If p regnant or breast-feeding, ask a doctor before use.

OTC - KEEP OUT OF REACH OF CHILDREN SECTION

Keep out of reach of children.